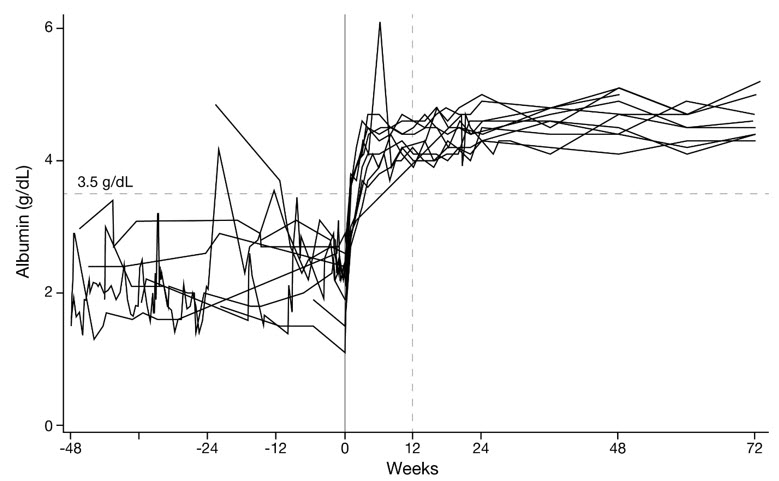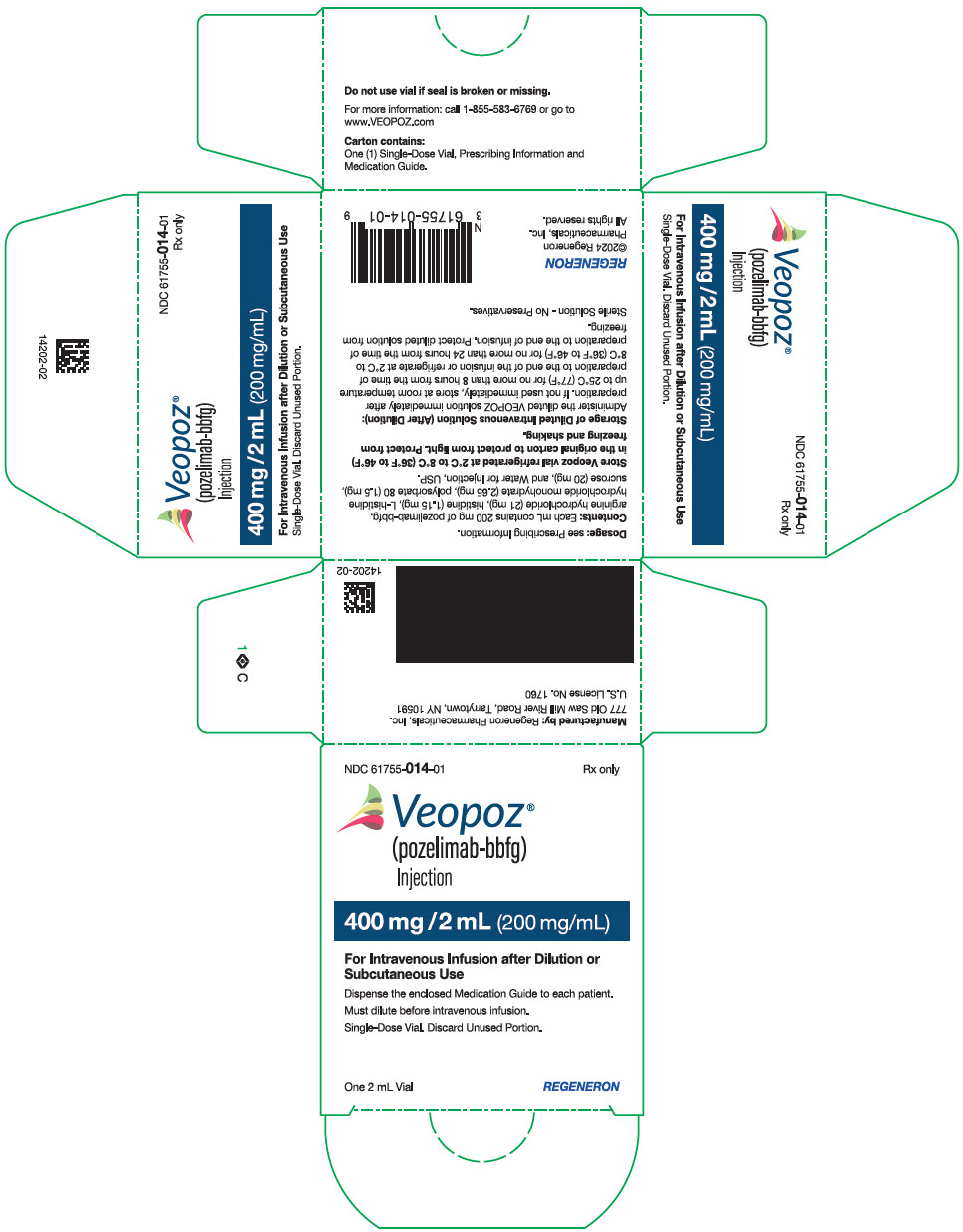 DRUG LABEL: VEOPOZ
NDC: 61755-014 | Form: INJECTION, SOLUTION
Manufacturer: Regeneron Pharmaceuticals, Inc.
Category: prescription | Type: HUMAN PRESCRIPTION DRUG LABEL
Date: 20251204

ACTIVE INGREDIENTS: Pozelimab 200 mg/1 mL
INACTIVE INGREDIENTS: HISTIDINE; HISTIDINE MONOHYDROCHLORIDE MONOHYDRATE; POLYSORBATE 80; sucrose; ARGININE HYDROCHLORIDE; Water

HIGHLIGHTS OF PRESCRIBING INFORMATION

These highlights do not include all the information needed to use VEOPOZ safely and effectively. See full prescribing information for VEOPOZ.
VEOPOZ® (pozelimab-bbfg) injection, for intravenous or subcutaneous use
Initial U.S. Approval: 2023

WARNING: SERIOUS MENINGOCOCCAL INFECTIONS

See full prescribing information for complete boxed warning

- Life-threatening and fatal meningococcal infections have occurred in patients treated with complement inhibitors. Meningococcal infection may become rapidly life-threatening or fatal if not recognized and treated early. (5.1)
- Complete or update meningococcal vaccination at least 2 weeks prior to administering the first dose of VEOPOZ, unless the risks of delaying therapy outweigh the risks of developing meningococcal infection. Follow the most current Advisory Committee on Immunization Practices (ACIP) recommendations for meningococcal vaccination in patients receiving a complement inhibitor. (5.1)
- Patients receiving VEOPOZ are at increased risk for invasive disease caused by N. meningitidis, even if they develop antibodies following vaccination. Monitor patients for early signs of meningococcal infections and evaluate immediately if infection is suspected. (5.1)

1 INDICATIONS AND USAGE

VEOPOZ is a complement inhibitor indicated for the treatment of adult and pediatric patients 1 year of age and older with CD55-deficient protein-losing enteropathy (PLE), also known as CHAPLE disease. (1)

2 DOSAGE AND ADMINISTRATION

See the full prescribing information for meningococcal vaccine and prophylaxis recommendations prior to the first dose of VEOPOZ. (2.1)

Recommended Dosage:

- Day 1 (loading dose): Administer a single 30 mg/kg dose by intravenous infusion after dilution. (2.2)
- Day 8 and thereafter (maintenance dosage): Inject 10 mg/kg as a subcutaneous injection once weekly starting on Day 8.
  - The maintenance dosage may be increased to 12 mg/kg once weekly if there is inadequate clinical response after at least 3 weekly doses (i.e., starting from Week 4).
  - The maximum maintenance dosage is 800 mg once weekly. (2.2)
- See full prescribing information for instructions on preparation and administration. (2.2, 2.3, 2.4)

3 DOSAGE FORMS AND STRENGTHS

Injection: 400 mg/2 mL (200 mg/mL) in a single-dose vial. (3)

4 CONTRAINDICATIONS

VEOPOZ is contraindicated in patients with unresolved Neisseria meningitidis infection. (4)

5 WARNINGS AND PRECAUTIONS

- Other Bacterial Infections: Interrupt treatment with VEOPOZ in patients who are undergoing treatment for a serious encapsulated bacterial infection until the infection is resolved. (5.2)
- Systemic Hypersensitivity Reactions: Interrupt infusion and institute appropriate supportive measures if signs of cardiovascular instability or respiratory compromise occur. (5.3)
- Immune Complex Formation: Transition between other complement inhibitors has resulted in decreased drug concentrations and possible hypersensitivity reactions. Consider this potential if switching complement inhibitors to VEOPOZ. (5.4)

6 ADVERSE REACTIONS

Most common adverse reactions (in two or more patients) are: upper respiratory tract infection, fracture, urticaria, and alopecia. (6.1)

To report SUSPECTED ADVERSE REACTIONS, contact Regeneron at 1-855-583-6769 or FDA at 1-800-FDA-1088 or www.fda.gov/medwatch.

7 DRUG INTERACTIONS

Intravenous Immunoglobulin: May decrease pozelimab concentrations; avoid concomitant use. If concomitant use cannot be avoided, monitor patients for worsening of clinical signs and symptoms of disease. (7.1)

FULL PRESCRIBING INFORMATION

WARNING: SERIOUS MENINGOCOCCAL INFECTIONS

- Life-threatening and fatal meningococcal infections have occurred in patients treated with complement inhibitors. Meningococcal infection may become rapidly life-threatening or fatal if not recognized and treated early.
- Complete or update meningococcal vaccination (for serogroups A, C, W and Y, and serogroup B) at least 2 weeks prior to administering the first dose of VEOPOZ, unless the risks of delaying therapy outweigh the risk of developing a meningococcal infection. Follow the most current Advisory Committee on Immunization Practices (ACIP) recommendations for meningococcal vaccination in patients receiving a complement inhibitor.
- Patients receiving VEOPOZ are at increased risk for invasive disease caused by N. meningitidis, even if they develop antibodies following vaccination. Monitor patients for early signs of meningococcal infections and evaluate immediately if infection is suspected [see Warnings and Precautions (5.1)].

1 INDICATIONS AND USAGE

VEOPOZ is indicated for the treatment of adult and pediatric patients 1 year of age and older with CD55-deficient protein-losing enteropathy (PLE), also known as CHAPLE disease.

2 DOSAGE AND ADMINISTRATION

2.1 Recommended Vaccination and Prophylaxis for Meningococcal Infection Prior to First Dose of VEOPOZ

- Vaccinate patients for meningococcal infection (serogroups A, C, W, and Y [MenACWY] and serogroup B [MenB]) according to current ACIP recommendations for patients receiving a complement inhibitor at least 2 weeks prior to administering the first dose of VEOPOZ [see Warnings and Precautions (5.1)].
- If urgent VEOPOZ therapy is indicated in a patient who is not up-to-date with vaccines for both MenACWY and MenB according to ACIP recommendations, administer meningococcal vaccine(s) as soon as possible and provide the patient with antibacterial drug prophylaxis. The efficacy, duration, and drug regimens for antibacterial drug prophylaxis have not been studied in patients receiving complement inhibitors, including VEOPOZ.

2.2 Recommended Dosage and Administration

The recommended dosage of VEOPOZ is as follows:

Day 1 (Loading Dose):

Administer a single 30 mg/kg dose by intravenous infusion after dilution [see Dosage and Administration (2.3)].

Day 8 and Thereafter (Maintenance Dosage):

Inject 10 mg/kg as a subcutaneous injection once weekly starting on Day 8 [see Dosage and Administration (2.4)].

- The maintenance dosage may be increased to 12 mg/kg once weekly if there is inadequate clinical response after at least 3 weekly doses (i.e., starting from Week 4).
- The maximum maintenance dosage is 800 mg once weekly.
- Doses greater than 400 mg require 2 injections.

2.3 Intravenous Infusion Loading Dose: Preparation and Administration Instructions

VEOPOZ for intravenous use must be prepared and administered by a healthcare provider.

Preparation Instructions for Intravenous Infusion Loading Dose

1. Remove VEOPOZ vial(s) from refrigeration and allow the vial(s) to sit for at least 45 minutes at room temperature 20ºC to 25ºC (68ºF to 77ºF) before use.
2. Parenteral drug products should be inspected visually for particulate matter and discoloration prior to administration, whenever solution and container permit. VEOPOZ should be a clear to slightly opalescent, colorless to pale yellow solution that is free from visible particulates. Discard the vial(s) if the solution is cloudy, discolored or contains particulate matter.
3. Gently swirl the vial(s) in an upright position. Do not shake the vial(s) as this may result in foaming.
4. Use a 21G stainless steel needle with Luer-Lok to withdraw the calculated volume of VEOPOZ from the vial(s). Discard any unused VEOPOZ remaining in the vial(s).
5. Dilute VEOPOZ in an intravenous infusion bag of 25 mL to 250 mL of either 0.9% Sodium Chloride Injection or 5% Dextrose Injection to a final concentration of 6.7 mg/mL to 20 mg/mL.
6. Mix the diluted solution by gentle inversion. Do not shake.

Administration Instructions for Intravenous Infusion Loading Dose

1. Infuse through an intravenous line containing a sterile, in-line or add-on 0.2-micron to 5-micron filter.
  - Infusion rate: infuse over a minimum of 1 hour; do not exceed maximum rate of 1000 mg/hour
  - Do not co-administer other medications through the same intravenous line
2. Observe the patient for 30 minutes following completion of the infusion [see Warnings and Precautions (5.3)].

Storage of Diluted Intravenous Solution

- Administer the diluted VEOPOZ solution immediately after preparation. If not used immediately, store at room temperature up to 25°C (77°F) for no more than 8 hours from the time of preparation to the end of the infusion or refrigerate at 2°C to 8°C (36°F to 46°F) for no more than 24 hours from the time of preparation to the end of infusion.
- If stored in the refrigerator, allow the diluted solution to come to room temperature prior to administration.
- Discard the unused VEOPOZ diluted solution after 8 hours if stored at room temperature or after 24 hours if refrigerated.
- Do not freeze the diluted solution.

2.4 Subcutaneous Maintenance Dose: Preparation and Administration Instructions

VEOPOZ for subcutaneous use must be prepared and administered by a healthcare provider.

Preparation Instructions for Subcutaneous Maintenance Dose

1. Remove VEOPOZ vial(s) from refrigeration and allow the vial(s) to sit for at least 45 minutes at room temperature 20ºC to 25ºC (68ºF to 77ºF) before use.
2. Parenteral drug products should be inspected visually for particulate matter and discoloration prior to administration, whenever solution and container permit. VEOPOZ should be a clear to slightly opalescent, colorless to pale yellow solution that is free from visible particulates. Discard the vial(s) if the solution is cloudy, discolored or contains particulate matter.
3. Gently swirl the vial(s) in an upright position. Do not shake the vial(s) as this may result in foaming.
4. Use a withdrawal needle (21G needle with Luer-Lok) to withdraw the calculated dose volume of VEOPOZ from the appropriate number of vial(s). Discard any unused VEOPOZ remaining in the vial(s).
  - For patients receiving a dose greater than 400 mg, preparation of 2 separate injections will be required for subcutaneous administration of the total dose volume.
5. Change the needle on the syringe to an injection needle fulfilling the following criteria: 25G to 27G and 1/2 or 5/8-inch stainless steel needle with Luer-Lok.

Administration Instructions for Subcutaneous Maintenance Dose

1. Inject VEOPOZ into the abdomen, thigh, or upper arm. Rotate sites. Do not inject VEOPOZ into moles, scars, or areas where the skin is tender, bruised, red, hard, or not intact. When administering more than one injection, administer consecutively, each at different injection sites.
2. Observe the patient for 30 minutes following completion of the first subcutaneous injection [see Warnings and Precautions (5.3)].

Storage of Subcutaneous Injection

Administer the subcutaneous injection within 4 hours of preparation.

2.5 Recommendations Regarding Missed Maintenance Subcutaneous Dose(s)

If a subcutaneous maintenance dose of VEOPOZ is missed, administer as soon as possible within 3 days after the missed dose. Do not administer 2 doses on the same day to make up for a missed dose. If more than 3 days have passed, skip the missed dose and administer the next dose on the regularly scheduled day. In each case, patients can then resume their regular once weekly dosing schedule.

The day of weekly administration can be changed, if necessary, as long as the time between the two doses is at least 4 days (96 hours).

3 DOSAGE FORMS AND STRENGTHS

Injection: 400 mg/2 mL (200 mg/mL) as a clear to slightly opalescent, colorless to pale yellow solution in a single-dose vial.

4 CONTRAINDICATIONS

VEOPOZ is contraindicated in:

- Patients with unresolved Neisseria meningitidis infection [see Warnings and Precautions (5.1)].

5 WARNINGS AND PRECAUTIONS

5.1 Serious Meningococcal Infections

Life-threatening and fatal meningococcal infections have occurred in both vaccinated and unvaccinated patients treated with complement inhibitors. The use of VEOPOZ increases a patient's susceptibility to serious and life-threatening meningococcal infections (septicemia and/or meningitis) caused by any serogroup, including nongroupable strains.

Complete or update meningococcal vaccination (for serogroups A, C, W, and Y [MenACWY] and serogroup B [MenB]) at least 2 weeks prior to administering the first dose of VEOPOZ, according to the most current Advisory Committee on Immunization Practices (ACIP) recommendations for patients receiving a complement inhibitor. Revaccinate patients in accordance with ACIP recommendations considering the duration of VEOPOZ therapy.

If urgent VEOPOZ therapy is indicated in a patient who is not up-to-date with both MenACWY and MenB vaccines according to ACIP recommendations, administer meningococcal vaccine(s) as soon as possible and provide the patient with antibacterial drug prophylaxis. The efficacy, duration, and drug regimens for antibacterial drug prophylaxis have not been studied in patients receiving complement inhibitors.

Because of inhibition of complement activity by VEOPOZ, as well as risk of infection caused by nongroupable strains of N. meningitidis, vaccination does not eliminate the risk of meningococcal infections, despite development of antibodies following vaccination.

Closely monitor patients for early signs and symptoms of meningococcal infection and evaluate patients immediately if infection is suspected. Inform patients and caregivers of these signs and symptoms and instruct patients to seek immediate medical care if these signs and symptoms occur. Meningococcal infection may become rapidly life-threatening or fatal if not recognized and treated early. Interrupt treatment with VEOPOZ in patients who are undergoing treatment for serious meningococcal infection until the infection is resolved [see Contraindications (4)].

5.2 Other Bacterial Infections

VEOPOZ blocks terminal complement activation; therefore, patients may have increased susceptibility to encapsulated bacterial infections, especially infections caused by Neisseria meningitidis but also Streptococcus pneumoniae, Haemophilus influenzae, and to a lesser extent, Neisseria gonorrhoeae. Patients treated with VEOPOZ may be at increased risk of developing serious infections due to Streptococcus pneumoniae and Haemophilus influenzae type b (Hib). Administer vaccinations for the prevention of Streptococcus pneumoniae and Haemophilus influenzae type b (Hib) infections according to ACIP guidelines. Patients receiving VEOPOZ are at increased risk for infections due to these organisms, even if they develop antibodies following vaccination. Interrupt treatment with VEOPOZ in patients who are undergoing treatment for a serious encapsulated bacterial infection until the infection is resolved. Counsel patients about gonorrhea prevention and advise regular testing for patients at risk.

5.3 Systemic Hypersensitivity Reactions

Hypersensitivity reactions, including anaphylaxis, have been reported with administration of complement inhibitors. Interrupt VEOPOZ and institute appropriate supportive measures if signs of cardiovascular instability or respiratory compromise occur.

5.4 Immune Complex Formation

Immune complex formation has been reported during the transition of therapy between complement inhibitors, resulting in transient decrease in drug concentrations as well as symptoms suggestive of hypersensitivity reactions. However, this has not been studied in patients with CD55-deficient PLE switching from other complement inhibitors to pozelimab. The potential for immune complex formation should be considered if switching complement inhibitors.

6 ADVERSE REACTIONS

The following clinically significant adverse reactions are described elsewhere in the labeling:

- Serious Meningococcal Infections [see Warnings and Precautions (5.1)]
- Other Bacterial Infections [see Warnings and Precautions (5.2)]
- Systemic Hypersensitivity Reactions [see Warnings and Precautions (5.3)]
- Immune Complex Formation [see Warnings and Precautions (5.4)]

6.1 Clinical Trials Experience

Because clinical trials are conducted under widely varying conditions, adverse reaction rates observed in the clinical trials of a drug cannot be directly compared to rates in the clinical trials of another drug and may not reflect the rates observed in practice.

The safety of VEOPOZ was evaluated in 10 patients with CD55-deficient PLE (ranging from 3 to 19 years of age) in a single-arm study [see Clinical Studies (14)]. The median duration of exposure was 104 weeks (range: 75 to 140 weeks). Adverse reactions reported in two or more patients are summarized in Table 1.

Table 1: Adverse Reactions Reported in Two or More VEOPOZ-Treated Patients with CD55-deficient PLE in a Clinical Trial
Adverse Reactions | VEOPOZ N=10 n (%)
Upper respiratory tract infection [Composed of similar terms] | 3 (30)
Fracture | 3 (30)
Urticaria | 2 (20)
Alopecia | 2 (20)

Additionally, injection site reactions (including dermatitis and erythema), metabolic acidosis, gingival bleeding, increased blood uric acid, increased liver enzymes, hematuria and proteinuria were reported in one patient each.

Vital Signs:

Four patients reported elevated systolic and/or diastolic blood pressure readings above the normal range for age at multiple study visits.

7 DRUG INTERACTIONS

7.1 Intravenous Immunoglobulin

VEOPOZ has not been studied in combination with intravenous immunoglobulin. Intravenous immunoglobulin may interfere with the endosomal neonatal Fc receptor (FcRn) recycling mechanism of monoclonal antibodies such as pozelimab thereby decreasing serum pozelimab concentrations. Avoid concomitant use of intravenous immunoglobulin with VEOPOZ. If concomitant use cannot be avoided, monitor patients for worsening of clinical signs and symptoms of CD55-deficient PLE [see Clinical Pharmacology (12.3)].

8 USE IN SPECIFIC POPULATIONS

8.1 Pregnancy

Risk Summary

Although there are no data on VEOPOZ use in pregnant women to inform a drug-associated risk of major birth defects, miscarriage, or adverse maternal or fetal outcomes, monoclonal antibodies can be actively transported across the placenta.

In an animal reproduction study in monkeys, pozelimab-bbfg did not adversely affect embryofetal or postnatal development when administered from pregnancy confirmation through parturition at doses that produced exposure up to 3.3 to 3.8 times the predicted clinical exposures (on an AUC basis; see Data).

The estimated background risk of major birth defects and miscarriage for the indicated population is unknown. All pregnancies have a background risk of birth defect, loss, or other outcome. In the U.S. general population, the estimated background risk of major birth defects and miscarriage in clinically recognized pregnancies is 2 to 4% and 15 to 20%, respectively.

Data

Animal Data

In an enhanced pre- and postnatal development study, pregnant female monkeys were subcutaneously administered pozelimab-bbfg at doses of 5 or 50 mg/kg once weekly from confirmation of pregnancy (gestation day 20) through parturition (approximately gestation day 160). No adverse effects were observed on maintenance of pregnancy, pregnancy outcome, or on the development of offspring through postnatal day 90 at doses up to 3.3-3.8 times the predicted clinical exposures.

8.2 Lactation

Risk Summary

There are no data on the presence of pozelimab-bbfg in either human or animal milk, the effects on the breastfed infant, or the effects on milk production. Endogenous maternal IgG and monoclonal antibodies are transferred into human milk. The effects of local gastrointestinal exposure and the extent of systemic exposure in the breastfed infant to pozelimab are unknown. The development and health benefits of breastfeeding should be considered along with the mother's clinical need for VEOPOZ and any potential adverse effects on the breastfed infant from VEOPOZ or from the underlying maternal condition.

8.4 Pediatric Use

The safety and effectiveness of VEOPOZ for the treatment of CD55-deficient PLE have been established in pediatric patients 1 year of age and older. Use of VEOPOZ for this indication is supported by a single-arm study in 10 patients with active CD55-deficient PLE [see Adverse Reactions (6.1) and Clinical Studies (14)].

The safety and effectiveness of VEOPOZ have not been established in pediatric patients less than 1 year of age.

8.5 Geriatric Use

CD55-deficient PLE is largely a disease of pediatric patients. VEOPOZ has not been studied in the geriatric population.

11 DESCRIPTION

Pozelimab-bbfg, a complement inhibitor, is a recombinant monoclonal antibody (IgG4 isotype). Pozelimab-bbfg is produced by recombinant DNA technology in Chinese Hamster Ovary (CHO) cell suspension culture and has an approximate molecular weight of 145 kDa.

VEOPOZ (pozelimab-bbfg) injection is a sterile, preservative-free, clear to slightly opalescent, colorless to pale yellow solution supplied in a single-dose glass vial, free from visible particulates, for intravenous or subcutaneous use. Each vial contains 400 mg pozelimab-bbfg in 2 mL of solution with a pH of 5.8. Each mL contains 200 mg pozelimab-bbfg, arginine hydrochloride (21 mg), histidine (1.15 mg), L-histidine hydrochloride monohydrate (2.65 mg), polysorbate 80 (1.5 mg), sucrose (20 mg), and Water for Injection, USP.

12 CLINICAL PHARMACOLOGY

12.1 Mechanism of Action

Pozelimab-bbfg is a human, monoclonal immunoglobulin G4P (IgG4P) antibody directed against the terminal complement protein C5 that inhibits terminal complement activation by blocking cleavage of C5 into C5a (anaphylatoxin) and C5b, thereby blocking the formation of the membrane-attack complex (C5b-C9, a structure mediating cell lysis).

12.2 Pharmacodynamics

The effect of pozelimab-bbfg on complement activity was measured by total complement hemolytic activity test (CH50). The magnitude and duration of reduction from baseline in CH50 by pozelimab-bbfg was dose dependent.

In healthy subjects receiving a single dose of VEOPOZ 30 mg/kg administered as an intravenous infusion over approximately one hour, the complete inhibition of CH50 was achieved at the end of infusion in all subjects, was maintained for 28 days, and returned to baseline 84 days post-dose. After a single dose of VEOPOZ administered as a 600 mg subcutaneous injection, the maximum reduction from baseline in CH50 was achieved 7 days post-dose in most subjects (range: 3 to 14 days), corresponding to Tmax, and returned to baseline 56 days post-dose.

In patients with CD55-deficient PLE receiving a single 30 mg/kg dose administered as an intravenous infusion over approximately one hour followed by a weight-tiered subcutaneous injection once weekly starting at Week 1, CH50 was completely inhibited by Week 1 for most subjects and by Week 12 for all patients.

In the same study of patients with CD55-deficient PLE, serum albumin concentrations increased as early as Week 1 and reached the normal range (≥3.5 g/dL) by Week 4 for most subjects and by Week 12 for all subjects. The serum albumin concentrations were maintained within the normal range for the duration of treatment. Endogenous serum IgG concentrations were also increased from baseline at Week 1 in all patients with CD55-deficient PLE and reached a stable concentration around Week 16 [see Clinical Studies (14)].

12.3 Pharmacokinetics

In healthy subjects, single intravenous infusions of VEOPOZ over approximately one hour resulted in dose proportional increases in mean Cmax, but greater than proportional increases in mean AUCinf (>16-fold) for total pozelimab concentrations in serum between 3 mg/kg and 30 mg/kg. The mean AUCinf increased by 3.5-fold between 10 mg/kg and 30 mg/kg. In healthy subjects, single subcutaneous injections of VEOPOZ resulted in approximately 1.5-fold increase in mean Cmax and 2.2-fold increase in mean AUCinf between 300 mg and 600 mg.

In patients with CD55-deficient PLE, a single dose of VEOPOZ 30 mg/kg administered as an intravenous infusion over approximately one hour resulted in median (range) total pozelimab trough concentration of 180 (52.8, 268) mg/L at Week 1. The predicted mean (SD) trough concentrations of total pozelimab at steady state are 330 (94.2) mg/L and 385 (112) mg/L for VEOPOZ 10 mg/kg or 12 mg/kg (up to a maximum 800 mg) once weekly via subcutaneous injection(s), respectively, following the intravenous loading dose.

Absorption

In healthy subjects, following subcutaneous injection of 600 mg, the bioavailability of pozelimab-bbfg is estimated as 51%. The median (range) time to reach peak concentration was 7 (3 to 7) days following a single subcutaneous injection of 300 mg or 600 mg in healthy subjects.

Distribution

In healthy adult subjects with a mean body weight of 70 kg, the mean (SD) volume of distribution following a single intravenous dose of 30 mg/kg was 3.3 (0.4) L. The mean (SD) apparent volume of distribution following a single subcutaneous injection of 300 mg and 600 mg was 6.0 (0.9) L and 8.6 (2.7) L, respectively.

Elimination

Pozelimab-bbfg is expected to be degraded into small peptides and amino acids via catabolic pathways in the same manner as endogenous IgG. Pozelimab-bbfg elimination is mediated via linear and non-linear pathways. At higher concentrations, pozelimab-bbfg elimination is primarily through the linear non-saturable proteolytic pathway, whereas at lower concentrations, the non-linear, saturable C5 target-mediated elimination predominates.

In healthy adult subjects, the median (range) terminal half-life of total pozelimab in serum was 13.5 (10.0, 17.2) days following a single 30 mg/kg dose administered as an intravenous infusion. The median (range) terminal half-life was 14.1 (8.6, 17.3) days following a single 600 mg subcutaneous injection.

In patients with CD55-deficient PLE, steady-state total pozelimab concentrations were reached at approximately 20 weeks following subcutaneous injection once weekly.

Specific Populations

Body Weight

Body weight was a significant covariate on the pharmacokinetics of pozelimab-bbfg.

Renal and Hepatic Impairment

Pozelimab-bbfg, a monoclonal antibody, is not likely to undergo renal or hepatic excretion.

Drug Interaction Studies

Drug interaction studies have not been conducted. Intravenous Immunoglobulin (IVIg) may interfere with the endosomal neonatal Fc receptor (FcRn) recycling mechanism of monoclonal antibodies such as pozelimab-bbfg, which may decrease serum pozelimab concentrations [see Drug Interactions (7.1)].

12.6 Immunogenicity

The observed incidence of anti-drug antibodies is highly dependent on the sensitivity and specificity of the assay. Differences in assay methods preclude meaningful comparisons of the incidence of anti-drug antibodies in the study described below with the incidence of anti-drug antibodies in other studies, including those of VEOPOZ or of other pozelimab products.

Nine of the 10 patients 3 years of age and older with CD55-deficient PLE in the clinical study were evaluable for anti-pozelimab antibodies. None of these patients developed anti-pozelimab-bbfg antibodies during the 48-week treatment with pozelimab-bbfg. There is insufficient information to characterize the effect of anti-drug antibodies on the pharmacokinetics, pharmacodynamics, safety, and/or effectiveness of pozelimab.

13 NONCLINICAL TOXICOLOGY

13.1 Carcinogenesis, Mutagenesis, Impairment of Fertility

Carcinogenesis and Mutagenesis

Carcinogenicity studies have not been conducted with pozelimab-bbfg. The mutagenic potential of pozelimab-bbfg has not been evaluated; however, monoclonal antibodies are not expected to alter DNA or chromosomes.

Impairment of Fertility

Fertility studies have not been conducted with pozelimab-bbfg. In a 6-month toxicity study in sexually-mature male and female monkeys, pozelimab-bbfg had no adverse effects on histological or functional markers of reproductive function (e.g., estrous cyclicity, testicular volume, ejaculate amount, total sperm count per ejaculate, sperm motility and morphology, and histology of reproductive organs) at doses up to 100 mg/kg/week (11.9 to 13.9-fold the predicted exposures at the recommended clinical doses, on an AUC basis).

14 CLINICAL STUDIES

The efficacy and safety of VEOPOZ were evaluated in a single-arm study (NCT04209634) where outcomes were compared to pre-treatment data in patients with active CD55-deficient protein-losing enteropathy (PLE) who had hypoalbuminemia. Diagnosis was based on a clinical history of PLE and with a confirmed genotype of biallelic CD55 loss-of-function mutation.

Active CD55-deficient PLE was defined as hypoalbuminemia (serum albumin concentration of ≤3.2 g/dL) with one or more of the following signs or symptoms within the last six months: abdominal pain, diarrhea, peripheral edema, or facial edema.

Patients received a single 30 mg/kg loading dose of VEOPOZ administered by intravenous infusion over approximately one hour, followed by a once weekly weight-tiered maintenance dosage, administered as a subcutaneous injection starting one week after the loading dose.

All patients received meningococcal vaccination prior to treatment with VEOPOZ and antibacterials for prophylaxis of meningococcal infection. Patients were permitted to receive additional therapies as part of standard of care. Use of other complement inhibitors was prohibited.

Ten patients ranging from 3 to 19 years of age (median of 8.5 years) were assessed for efficacy. Six patients identified as female; seven patients as White, two patients as Asian, and one patient reported race as other. The mean baseline serum albumin concentration was 2.2 g/dL with a range of 1.1 to 2.9 g/dL.

Serum Albumin Concentrations

The median time for serum albumin to reach at least 3.5 g/dL was 15.5 days (N=10; 95% CI: 8 to 28). All 10 patients achieved normalization by Week 12 and maintained serum albumin concentrations within the normal range through at least 72 weeks of treatment (Figure 1).

Figure 1: Serum Albumin Concentrations from 48 Weeks Pre-Treatment Through 72 Weeks on VEOPOZ in Ten Patients with CD55-Deficient PLE

Albumin Transfusions

Five of the 10 patients received a total of 60 transfusions in the 48 weeks prior to treatment. In the 48 weeks after starting treatment, one patient received one albumin transfusion.

Hospitalizations

Nine of the 10 patients were hospitalized for a total of 268 days in the 48 weeks prior to treatment. In the 48 weeks after starting treatment, two patients were hospitalized for a total of 7 days.

Additional Efficacy Results

Serum IgG concentrations reached normal values for age in all patients within the first 12 weeks of treatment; improvement was maintained through at least 72 weeks of treatment.

16 HOW SUPPLIED/STORAGE AND HANDLING

VEOPOZ (pozelimab-bbfg) injection is a clear to slightly opalescent, colorless to pale yellow solution. It is supplied in a carton containing one single-dose glass vial of:

- 400 mg/2 mL (200 mg/mL) (NDC 61755-014-01).

STORAGE AND HANDLING

Store VEOPOZ vial refrigerated at 2°C to 8°C (36°F to 46°F) in the original carton to protect from light. Do not freeze. Do not shake. Discard unused portion.

17 PATIENT COUNSELING INFORMATION

Advise the patient to read the FDA-approved patient labeling (Medication Guide).

Inform patients that they will be given a Patient Safety Card for VEOPOZ that they should carry with them at all times. This card describes symptoms of meningococcal, or other infection, which, if experienced, should prompt the patient to seek immediate medical evaluation.

Meningococcal Infection

- Advise patients of the risk of meningococcal, and other bacterial infections.
- Inform patients of the need to complete or update meningococcal vaccination for both MenACWY and MenB at least 2 weeks prior to receiving the first dose of VEOPOZ and to be revaccinated according to current ACIP recommendations for meningococcal vaccines while on VEOPOZ therapy.
- Inform patients that vaccination may not prevent meningococcal infection.
- Inform patients of the signs and symptoms of meningococcal infection and advise patients to seek immediate medical attention if any signs or symptoms of infection occur [see Warnings and Precautions (5.1)].

Other Bacterial Infections, Including Gonococcal Infection

- Inform patients of the increased risk of other bacterial infections, particularly those due to encapsulated bacteria.
- Inform patients of the need to receive vaccinations according to the ACIP recommendations.
- Advise patients to report any new signs and symptoms of infection.
- Counsel patients about gonorrhea prevention and advise patients at risk (e.g., sexually active) to seek regular testing [see Warnings and Precautions (5.2)].

Systemic Hypersensitivity Reactions

Advise patients to notify the healthcare provider and seek immediate medical attention if they experience any symptoms of systemic hypersensitivity reactions [see Warnings and Precautions (5.3)].

Manufactured by:

Regeneron Pharmaceuticals, Inc.
777 Old Saw Mill River Road
Tarrytown, NY 10591-6707
U.S. License No. 1760

Marketed by:

Regeneron Pharmaceuticals, Inc. (Tarrytown, NY 10591)
©2024 Regeneron Pharmaceuticals, Inc.

All rights reserved.

MEDICATION GUIDE
VEOPOZ® (VEE-oh-poz)
(pozelimab-bbfg)
injection, for intravenous or subcutaneous use

What is the most important information I should know about VEOPOZ?
VEOPOZ is a medicine that affects your immune system. VEOPOZ can lower the ability of your immune system to fight infections.

- VEOPOZ increases your chance of getting serious and life-threatening meningococcal infections. Meningococcal infections may quickly become life-threatening and cause death if not recognized and treated early.

1. You must receive meningococcal vaccines at least 2 weeks before your first dose of VEOPOZ if you have not already had these vaccines.
2. If you had a meningococcal vaccine in the past, you might need additional vaccination before starting VEOPOZ. Your healthcare provider will decide if you need additional meningococcal vaccination.
3. If your healthcare provider decided that urgent treatment with VEOPOZ is needed, and your meningococcal vaccines are not up-to-date, you should receive meningococcal vaccination as soon as possible. You should also receive antibiotics.
4. Meningococcal vaccines reduce the risk of meningococcal infection but do not prevent all meningococcal infections. Call your healthcare provider or get emergency medical care right away if you get any of these signs and symptoms of a meningococcal infection:

- headache with nausea or vomiting
- headache with a stiff neck or stiff back
- fever and a rash
- muscle aches with flu-like symptoms

- headache and fever
- fever
- confusion
- eyes sensitive to light

Your healthcare provider will give you a Patient Safety Card about the symptoms of meningococcal, or other infection. Carry it with you at all times during treatment and for 3 months after your last VEOPOZ dose. Your risk of meningococcal infection may continue for several weeks after your last dose of VEOPOZ. It is important to show this card to any healthcare provider who treats you. This will help them diagnose and treat you quickly.
VEOPOZ may also increase the risk of other types of serious bacterial infections.

- People who take VEOPOZ may have an increased risk of getting infections caused by Streptococcus pneumoniae and Haemophilus influenzae.
- Certain people may also have an increased risk of bacterial infections including gonorrhea infection. Talk to your healthcare provider to find out if you are at risk of gonorrhea infection, about gonorrhea prevention, and regular testing.

Call your healthcare provider right away if you have any new signs or symptoms of infection.

What is VEOPOZ?
VEOPOZ is a prescription medicine called a monoclonal antibody. VEOPOZ is used to treat adults and children 1 year of age and older with a disease called CD55-deficient protein-losing enteropathy (PLE), also known as CHAPLE disease.
It is not known if VEOPOZ is safe and effective in children younger than 1 year of age.

Do not receive VEOPOZ if you:

- have a meningococcal infection.

Before you receive VEOPOZ, tell your healthcare provider about all of your medical conditions, including if you:

- have an infection or fever.
- are pregnant or plan to become pregnant. It is not known if VEOPOZ will harm your unborn baby.
- are breastfeeding or plan to breastfeed. It is not known if VEOPOZ passes into your breast milk. Talk to your healthcare provider about the best way to feed your baby during treatment with VEOPOZ.

Tell your healthcare provider about all the medicines you take, including prescription and over-the-counter medicines, vitamins, and herbal supplements.
It is important that you:

- have all recommended vaccinations before you start VEOPOZ.
- receive antibiotics if you start VEOPOZ within 2 weeks of receiving meningococcal vaccination.
- stay up to date with all recommended vaccinations during treatment with VEOPOZ.

VEOPOZ and other medicines may affect each other causing side effects. VEOPOZ may affect the way other medicines work, and other medicines may affect how VEOPOZ works.
Especially tell your healthcare provider if you take Intravenous Immunoglobulin (IVIg).
Know the medicines you take and the vaccines you receive. Keep a list of them to show your healthcare provider and pharmacist when you get a new medicine.

How should I receive VEOPOZ?

- The first dose of VEOPOZ is given through a vein (I.V. or intravenous infusion) usually over 1 hour or more, depending on your weight. If you have an allergic reaction during your VEOPOZ infusion, your healthcare provider may decide to give VEOPOZ more slowly or stop your infusion.
- You will then receive VEOPOZ one time each week starting on day 8 after the first dose, as an injection under the skin (subcutaneous injection).
- After the infusion and your first subcutaneous injection, you will be monitored for 30 minutes for allergic reactions.
- If you miss receiving a VEOPOZ subcutaneous dose, call your healthcare provider right away to find out when you will receive your next injection.

What are the possible side effects of VEOPOZ?
VEOPOZ can cause serious side effects including:

- See "What is the most important information I should know about VEOPOZ?"
- Allergic (hypersensitivity) reactions. Allergic reactions, including infusion-related reactions, may happen during your VEOPOZ intravenous or subcutaneous treatment. Tell your healthcare provider right away if you develop the following symptoms, or any other symptoms during your VEOPOZ treatment that may mean you are having a serious allergic reaction:

- chest pain
- trouble breathing or shortness of breath

- swelling of your face, tongue, or throat
- feel faint or pass out

The most common side effects of VEOPOZ are:

- upper respiratory tract infection
- hair loss (alopecia)

- fracture

- raised, red patches of skin that are often very itchy (hives)

Tell your healthcare provider if you have any side effect that bothers you or that does not go away. These are not all of the possible side effects of VEOPOZ. Call your doctor for medical advice about side effects. You may report side effects to FDA at 1-800-FDA-1088.

General information about the safe and effective use of VEOPOZ.
Medicines are sometimes prescribed for purposes other than those listed in a Medication Guide. You can ask your pharmacist or healthcare provider for information about VEOPOZ that is written for health professionals.

What are the ingredients in VEOPOZ?
Active ingredient: pozelimab-bbfg.
Inactive ingredients: arginine hydrochloride, histidine, L-histidine hydrochloride monohydrate, polysorbate 80, sucrose, and Water for Injection.
Manufactured by:
Regeneron Pharmaceuticals, Inc., Tarrytown, NY 10591 U.S. License No. 1760
© 2024 Regeneron Pharmaceuticals, Inc.
All rights reserved.
For more information about VEOPOZ, go to www.VEOPOZ.com or call 1-855-5VEOPOZ (1-855-583-6769).

This Medication Guide has been approved by the U.S. Food and Drug Administration.

Revised: March 2024

PRINCIPAL DISPLAY PANEL - 2 mL Vial Carton

NDC 61755-014-01

Rx only

Veopoz®
(pozelimab-bbfg)
Injection

400 mg/2 mL (200 mg/mL)

For Intravenous Infusion after Dilution or
Subcutaneous Use

Dispense the enclosed Medication Guide to each patient.

Must dilute before intravenous infusion.

Single-Dose Vial. Discard Unused Portion.

One 2 mL Vial

REGENERON